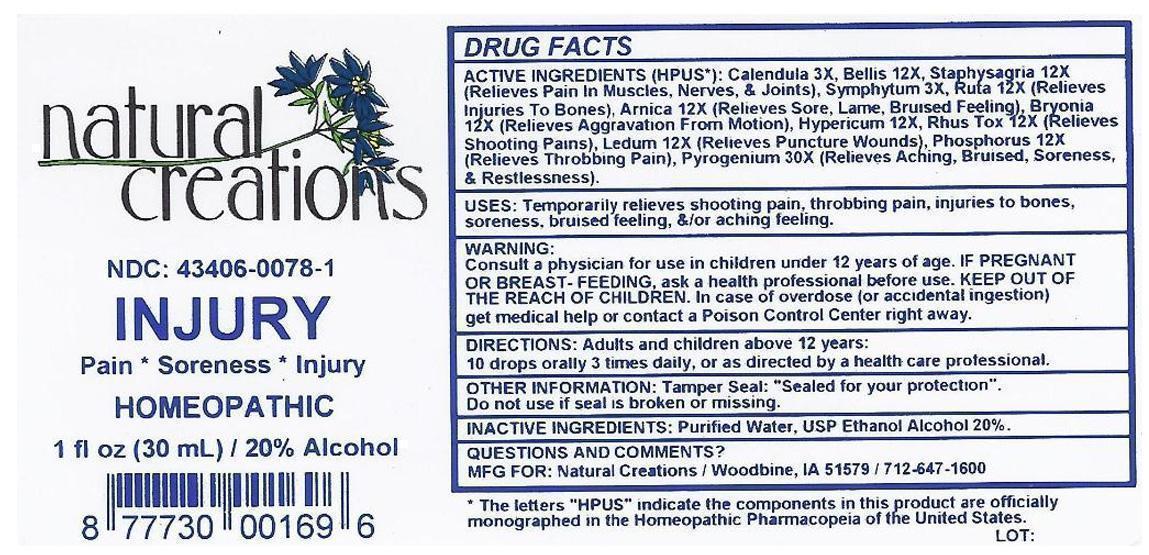 DRUG LABEL: INJURY
NDC: 43406-0078 | Form: LIQUID
Manufacturer: Natural Creations, Inc.
Category: homeopathic | Type: HUMAN OTC DRUG LABEL
Date: 20130201

ACTIVE INGREDIENTS: CALENDULA OFFICINALIS FLOWERING TOP 3 [hp_X]/1 mL; COMFREY ROOT 3 [hp_X]/1 mL; ARNICA MONTANA 12 [hp_X]/1 mL; BELLIS PERENNIS 12 [hp_X]/1 mL; BRYONIA ALBA ROOT 12 [hp_X]/1 mL; HYPERICUM PERFORATUM 12 [hp_X]/1 mL; LEDUM PALUSTRE TWIG 12 [hp_X]/1 mL; PHOSPHORUS 12 [hp_X]/1 mL; TOXICODENDRON PUBESCENS LEAF 12 [hp_X]/1 mL; RUTA GRAVEOLENS FLOWERING TOP 12 [hp_X]/1 mL; DELPHINIUM STAPHISAGRIA SEED 12 [hp_X]/1 mL; RANCID BEEF 30 [hp_X]/1 mL
INACTIVE INGREDIENTS: WATER; ALCOHOL

INJURY

ACTIVE INGREDIENT

ACTIVE INGREDIENTS (HPUS*): Calendula Officinalis 3X, Symphytum Officinale 3X, Arnica Montana 12X, Bellis Perennis 12X, Bryonia Alba 12X, Hypericum Perforatum 12X, Ledum Palustre 12X, Phosphorus 12X, Rhus Toxicodendron 12X, Ruta Graveolens 12X, Staphysagria 12X, Pyrogenium 30X.

PURPOSE

USES: Temporarily relieves shooting pain, throbbing pain, injuries to bones, soreness, bruised feeling, &/or aching feeling.

KEEP OUT OF REACH OF CHILDREN

KEEP OUT OF THE REACH OF CHILDREN. In case of overdose (or accidental ingestion) get medical help or contact a Poison Control Center.

INDICATIONS AND USAGE

USES: Temporarily relieves shooting pain, throbbing pain, injuries to bones, soreness, bruised feeling, &/or aching feeling.

WARNING:

Consult a physician for use in children under 12 years of age. IF PREGNANT OR BREAST-FEEDING, ask a health care professional before use. KEEP OUT OF THE REACH OF CHILDREN. In case of overdose (or accidental ingestion get medical help or contact a Poison Control Center right away.

DOSAGE AND ADMINISTRATION

DIRECTIONS: Adults and children above 12 years:

10 drops orally 3 times daily, or as directed by a health care professional.

INACTIVE INGREDIENTS: Purified Water, USP Ethanol Alcohol 20%.

PACKAGE LABEL

NDC: 43406-0078-1

INJURY

Pain * Soreness* Injury

HOMEOPATHIC

1 fl oz (30 mL) / 20% Alcohol

UPC: 877730001696